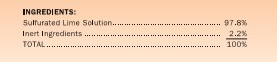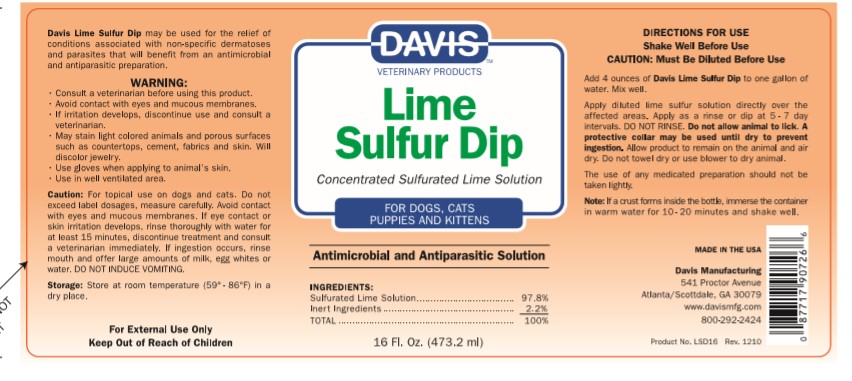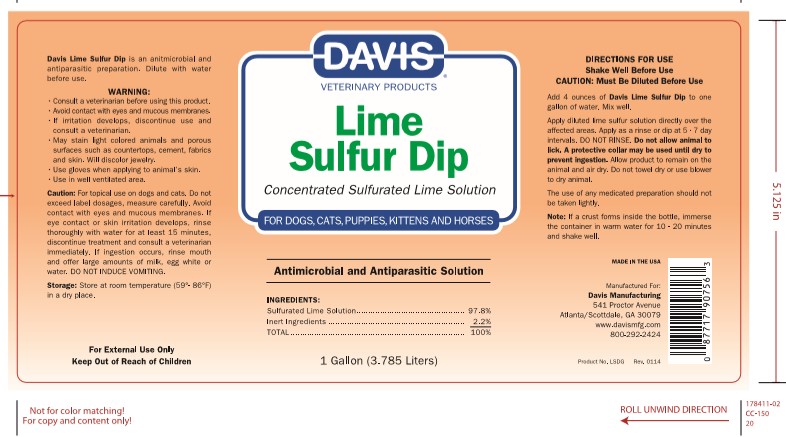 DRUG LABEL: Davis Lime Sulfur
NDC: 62570-050 | Form: SOLUTION, CONCENTRATE
Manufacturer: Davis Manufacturing and Packaging
Category: animal | Type: OTC ANIMAL DRUG LABEL
Date: 20191017

ACTIVE INGREDIENTS: CALCIUM POLYSULFIDE 25000 mg/1 g
INACTIVE INGREDIENTS: Water

Davis Lime Sulfur Dip

DESCRIPTION

Davis Lime Sulfur Dip isan antimicrobial and antiparasitic preparation. Dilute with water before use.

WARNINGS

- Consult a veterinarian befor using this product.
- Avoid contact with eyes and mucous membranes.
- If irritation develops, discontinue use and consult a veterinarian.
- May stain light colored animals and porous surfaces such as countertops, cement, fabrics and skin. Will discolor jewelry.
- Use gloves when applying to animal's skin.
- Use in well ventilated area.

PRECAUTIONS

Caution: For topical use on dogs and cats.

Do not exceed label dosages, measure carefully.

Avoid contact with eyes and mucous membrabes.

If eye contact or skin irritation develops, rinse thouroughly with water for 15 minutes,

discontinue treatment and consult a veterinarian immediately.

If ingestion occurs, rinse mouth and offer large amounts of milk, egg white, or water.

DO NOT INDUCE VOMITING.

STORAGE AND HANDLING

Storage: Store at room temerature (59°-86°F) in a dry place.

KEEP OUT OF REACH OF CHILDREN

For External use only

Keep out of reach of children

DOSAGE AND ADMINISTRATION

DIRECTIONS FOR USE

SHAKE WELL BEFORE USE

CAUTION: MUST BE DILUTED BEFORE USE

ADD 4 OUNCES OF DAVIS LIME SULFUR DIP TO ONE GALLON OF WATER. MIX WELL.

APPLY DILUTED LIME SULFUR SOLUTION DIRECTLY OVER THE AFFECTED AREAS.

APPLY AS A RINSE OR DIP AT 5-7 DAY INTERVALS.

DO NOT RINSE

DO NOT ALLOW ANIMAL TO LICK. A PROTECTIVE COLLAR MAY BE USED UNTIL DRY TO

PREVENT INGESTION. ALLOW PRODUCT TO REMAIN ON THE ANIMAL AND AIR DRY.

DO NOT TOWEL DRY OR USE A BLOWER TO DRY ANIMAL.

GENERAL PRECAUTIONS

THE USE OF ANY MEDICATED PREPARATION SHOULD NOT BE TAKEN LIGHTLY.

CLEANING, DISINFECTING, AND STERILIZATION INSTRUCTIONS

IF A CRUST FORMS INSIDE THE BOTTLE, IMMERSE THE CONTAINER IN WARM WATER FOR 10-20 MINUTES

SHAKE WELL.

MADE IN THE USA

MANUFACTURED FOR

DAVIS MANUFACTURING

541 PROCTOR AVENUE

ATLANTA/ SCOTTDALE, ga 30079

WWW.DAVISMFG.COM

800-292-2424

PACKAGE LABEL

DAVIS VETERINARY PRODUCTS

LIME SULFUR DIP

CONCENTRATED SULFURATED LIME SOLUTION

FOR DOGS, CATS, PUPPIES, KITTENS AND HORSES

ANTIMICROBIAL AND ANTIPARASITIC SOLUTION